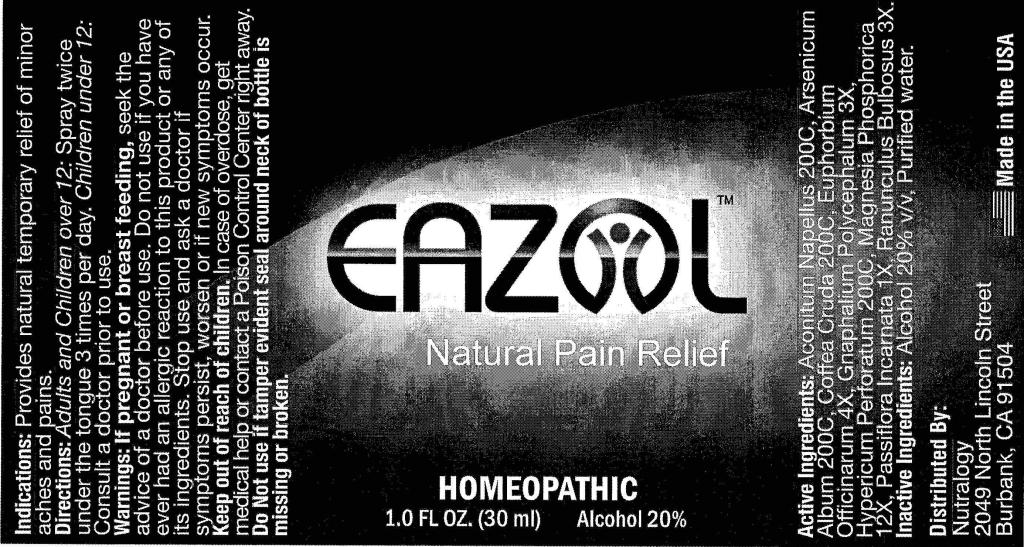 DRUG LABEL: Eazol
NDC: 50845-0131 | Form: SPRAY
Manufacturer: Liddell Laboratories, Inc.
Category: homeopathic | Type: HUMAN OTC DRUG LABEL
Date: 20110415

ACTIVE INGREDIENTS: ACONITUM NAPELLUS 200 [hp_C]/1 mL; ARSENIC TRIOXIDE 200 [hp_C]/1 mL; ARABICA COFFEE BEAN 200 [hp_C]/1 mL; EUPHORBIA RESINIFERA RESIN 4 [hp_X]/1 mL; PSEUDOGNAPHALIUM OBTUSIFOLIUM 3 [hp_X]/1 mL; HYPERICUM PERFORATUM 200 [hp_C]/1 mL; MAGNESIUM PHOSPHATE, DIBASIC TRIHYDRATE 12 [hp_X]/1 mL; PASSIFLORA INCARNATA TOP 1 [hp_X]/1 mL; RANUNCULUS BULBOSUS 3 [hp_X]/1 mL
INACTIVE INGREDIENTS: WATER; ALCOHOL

Eazol

ACTIVE INGREDIENT

ACTIVE INGREDIENTS: Aconitum napellus 200C, Arsenicum album 200C, Coffea cruda 200C, Euphorbium officinarum 4X, Gnaphalium polycephalum 3X, Hypericum perforatum 200C, Magnesia phosphorica 12X, Passiflora incarnata 1X, Ranunculus bulbosus 3X.

PURPOSE

INDICATIONS: Provides natural temporary relief of minor aches and pains.

WARNINGS

WARNINGS: If pregnant or breast feeding, seek the advice of a doctor before use.

Do not use if you have ever had an allergic reaction to this product or any of its ingredients.

Stop use and ask a doctor is symptoms persist, worsen or if new symptoms occur.

Keep out of reach of children. In case of overdose, get medical help or contact a Poison Control Center right away.

Do Not use if tamper evident seal around neck of bottle is missing or broken.

DOSAGE AND ADMINISTRATION

DIRECTIONS: Adults and Children over 12: Spray twice under the tongue 3 times per day. Children under 12: Consult a doctor prior to use.

INACTIVE INGREDIENTS: Alcohol 20% v/v, Purified water.

KEEP OUT OF REACH OF CHILDREN. In case of overdose, get medical help or contact a Poison Control Center right away.

INDICATIONS AND USAGE

INDICATIONS: Provides natural temporary relief of minor aches and pains.

QUESTIONS

Distributed By:

Nutralogy

2049 North Lincoln Street

Burbank, CA 91504

Made in the USA

PACKAGE LABEL

EAZOL

Natural Pain Relief

HOMEOPATHIC

1.0 FL OZ (30 ml)